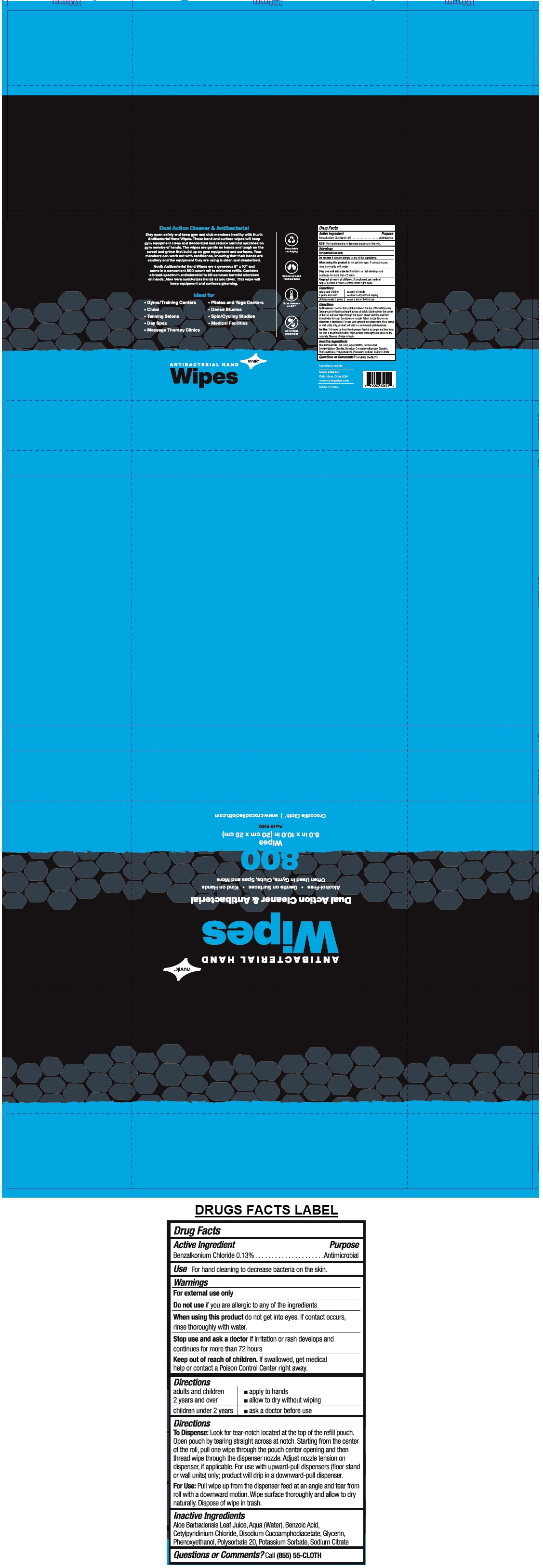 DRUG LABEL: Nuvik Large Roll Antibacterial Hand Wipes
NDC: 74602-800 | Form: CLOTH
Manufacturer: Nuvik Usa, Inc.
Category: otc | Type: HUMAN OTC DRUG LABEL
Date: 20200702

ACTIVE INGREDIENTS: BENZALKONIUM CHLORIDE 0.13 g/100 g
INACTIVE INGREDIENTS: ALOE VERA LEAF; WATER; BENZOIC ACID; CETYLPYRIDINIUM CHLORIDE; DISODIUM COCOAMPHODIACETATE; GLYCERIN; PHENOXYETHANOL; POLYSORBATE 20; POTASSIUM SORBATE; SODIUM CITRATE, UNSPECIFIED FORM

nuvik ANTIBACTERIAL HAND Wipes

Active Ingredient

Benzalkonium Chloride 0.13%

Purpose

Antimicrobial

Use

For hand cleaning to decrease bacteria on skin.

Warnings

For external use only

Do not use if you are allergic to any of the ingredients

When using this product do not get into eyes. If contact occurs, rinse thoroughly with water.

Stop use and ask a doctor if irritation or rash develops and continues for more than 72 hours

Keep out of reach of children. If swallowed, get medical help or contact a Poison Control Center right away.

Directions

adults and children 2 years and over | ▪ apply to hands ▪ allow to dry without wiping
children under 2 years | ▪ ask a doctor before use

To Dispense: Look for tear-notch located at the top of the refill pouch. Open pouch by tearing straight across at notch. Starting from the center of the roll, pull one wipe through the pouch center opening and then thread wipe through the dispenser nozzle. Adjust nozzle tension on dispenser, if applicable. For use with upward-pull dispensers (floor stand or wall units) only; product will drip in a downward-pull dispenser.

For Use: Pull wipe up from the dispenser feed at an angle and tear from roll with a downward motion. Wipe surface thoroughly and allow to dry naturally. Dispose of wipe in trash.

Inactive Ingredients

Aloe Barbadensis Leaf Juice, Aqua (Water), Benzoic Acid, Cetylpyridinium Chloride, Disodium Cocoamphodiacetate, Glycerin, Phenoxyethanol, Polysorbate 20, Potassium Sorbate, Sodium Citrate

Questions or Comments?

Call (855) 55- CLOTH

Dual Action Cleaner & Antibacterial

Alcohol-Free • Gentle on surfaces • Kind on Hands

Often Used in Gyms, Clubs, Spas and More

Crocodile Cloth® | www.crocodilecloth.com

Stay open safely and keep gym and club members healthy with Nuvik Antibacterial Hand Wipes. These hand and surfaces wipes will keep gym equipment clean and deodorized and reduce harmful microbes on gym memebers' hands. The wipes are gentle on hands and tough on the sweat and grime that build up on gym equipment and surfaces. Your members can work out with confidence, knowing that their hands are sanitary and the equipment they are using is clean and deodorized.

Nuvik Antibacterial Hand Wipes are a generous 8" x 10" and come in a convenient 800-count roll to minimize refills. Contains a broad-spectrum antimicrobial to kill common harmful microbes on hands. Aloe Vera moisturizes hands as you clean. This wipe will keep equipment and surfaces gleaming.

Ideal for

▪ Gyms/Training Centers

▪ Clubs

▪ Tanning Salons

▪ Day Spas

▪ Massage Therapy Clinics

▪ Pilates and Yoga Centers

▪ Dance Studios

▪ Spin/Cycling Studios

▪ Medical Facilites

Recyclable packaging

Safe on skin and most surfaces

Store between 40-75°F

Do not flush used wipes

Manufactured for:

Nuvik USA Inc

Columbus, Ohio, USA

www.nuvikglobal.com

Made in China